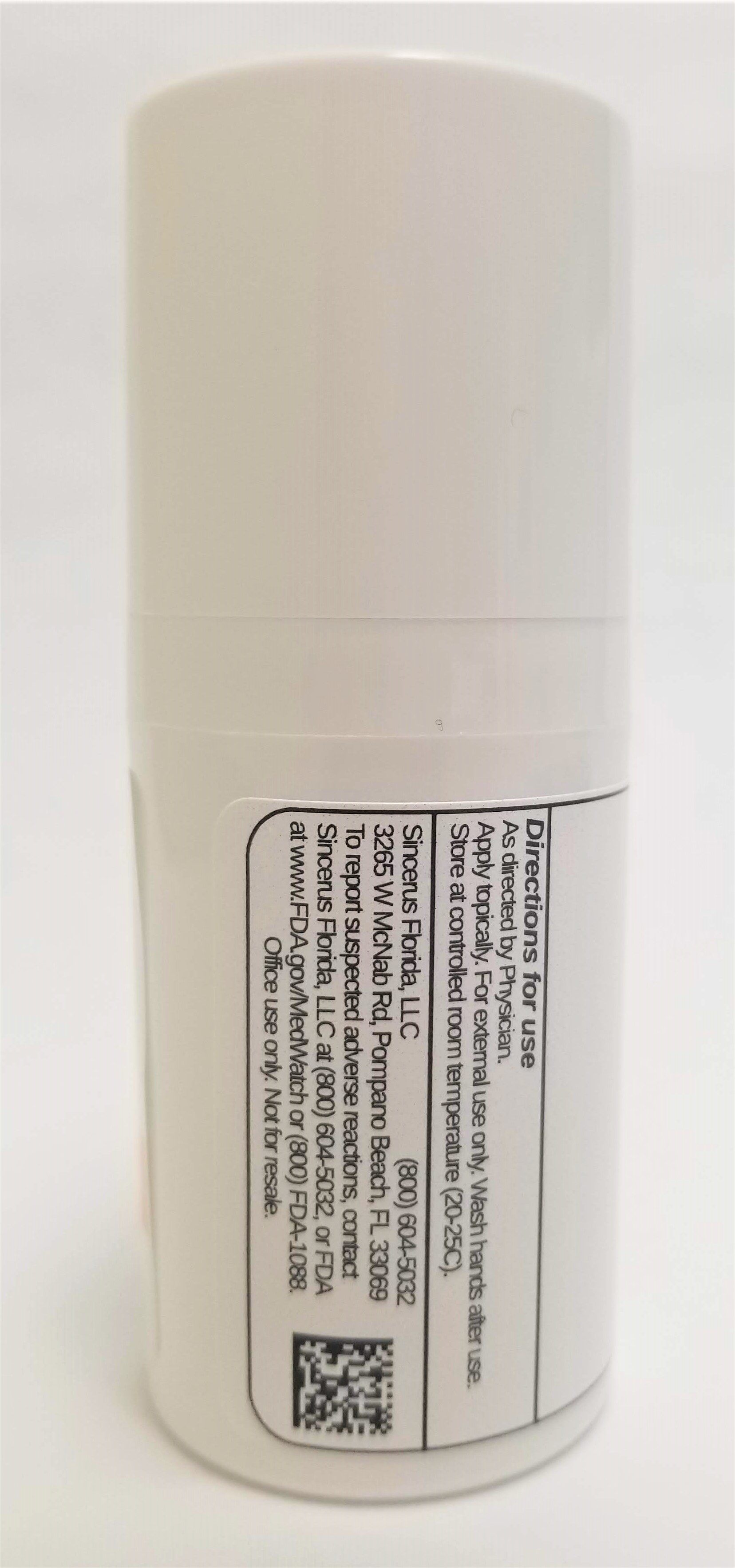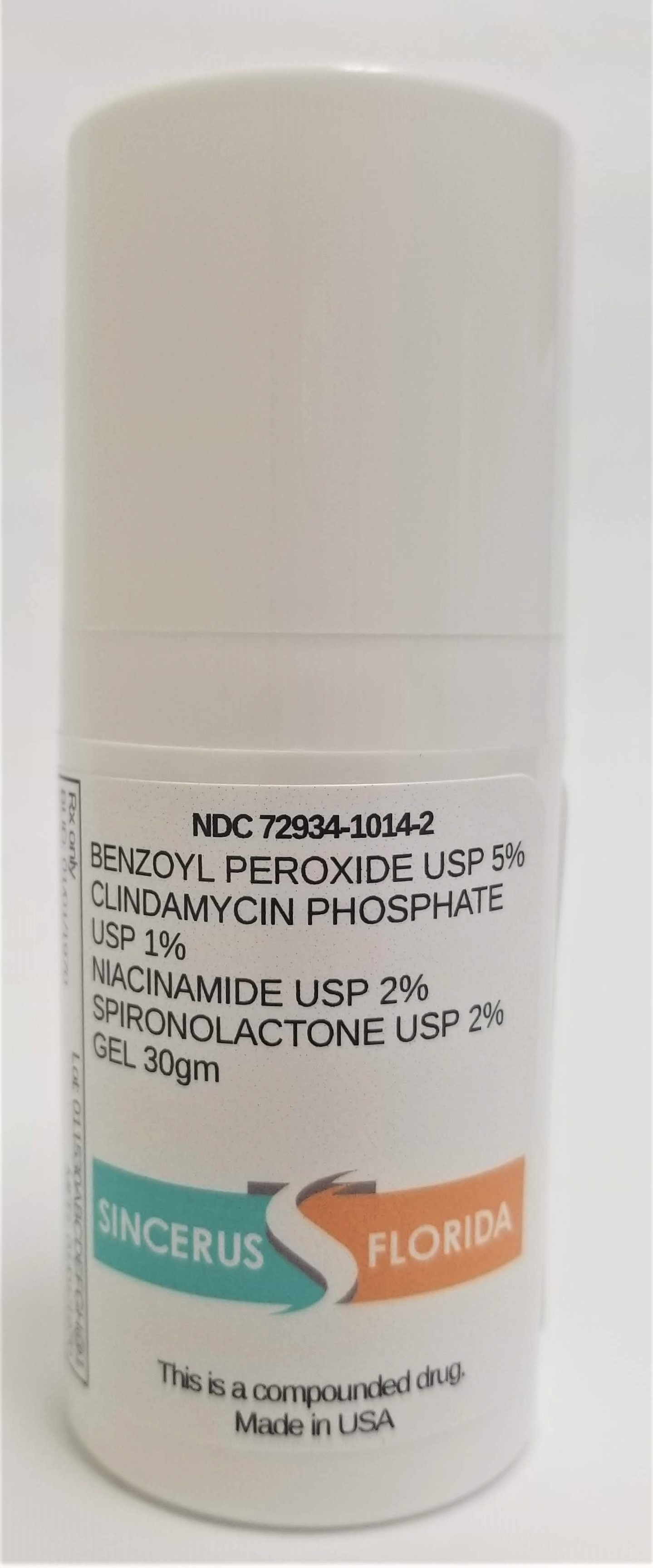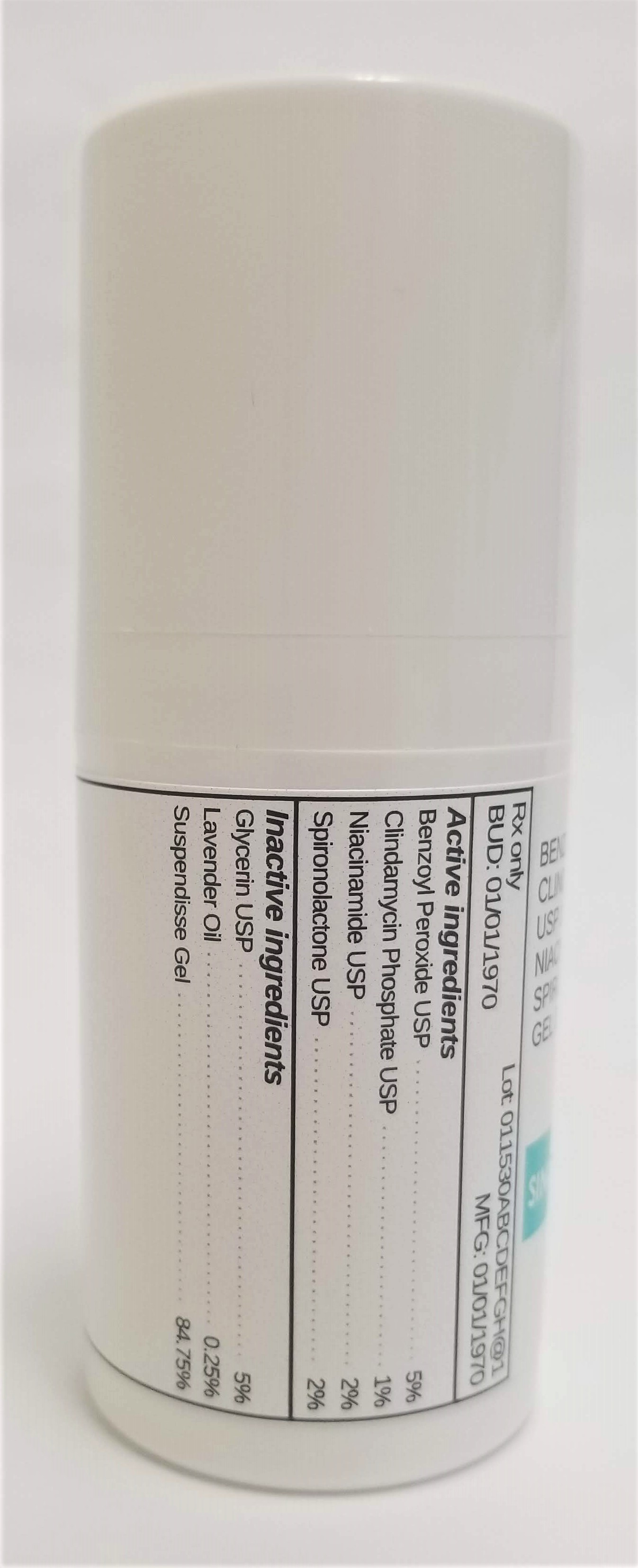 DRUG LABEL: BENZOYL PEROXIDE 5% / CLINDAMYCIN 1% / NIACINAMIDE 2% / SPIRONOLACTONE 2%
NDC: 72934-1014 | Form: GEL
Manufacturer: Sincerus Florida, LLC
Category: prescription | Type: HUMAN PRESCRIPTION DRUG LABEL
Date: 20190510

ACTIVE INGREDIENTS: BENZOYL PEROXIDE 5 g/100 g; CLINDAMYCIN PHOSPHATE 1 g/100 g; NIACINAMIDE 2 g/100 g; SPIRONOLACTONE 2 g/100 g

BENZOYL PEROXIDE 5% / CLINDAMYCIN 1% / NIACINAMIDE 2% / SPIRONOLACTONE 2%